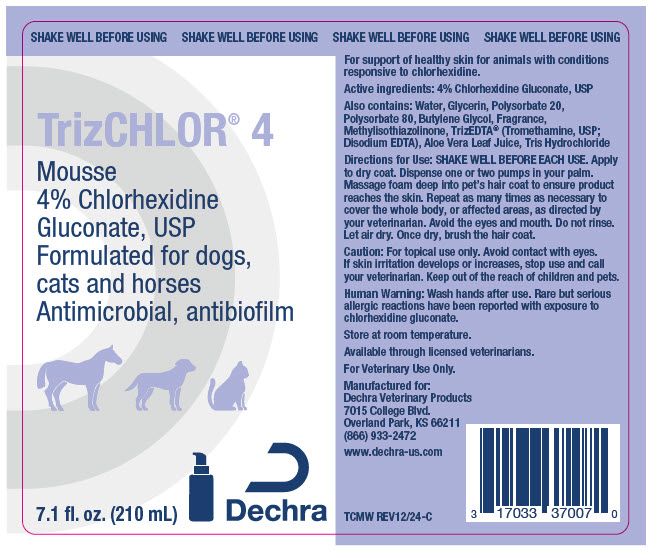 DRUG LABEL: TrizCHLOR 4 Mousse
NDC: 17033-371 | Form: SOLUTION
Manufacturer: Dechra Veterinary Products, LLC
Category: animal | Type: OTC ANIMAL DRUG LABEL
Date: 20241217

ACTIVE INGREDIENTS: Chlorhexidine Gluconate 40 mg/1 mL

TrizCHLOR® 4 Mousse

VETERINARY INDICATIONS

For support of healthy skin for animals with conditions responsive to chlorhexidine.

DESCRIPTION

Active ingredients: 4% Chlorhexidine Gluconate, USP

Also contains: Water, Glycerin, Polysorbate 20, Polysorbate 80, Butylene Glycol, Fragrance, Methylisothiazolinone, TrizEDTA® (Tromethamine, USP; Disodium EDTA), Aloe Vera Leaf Juice, Tris Hydrochloride

DOSAGE AND ADMINISTRATION

Directions for Use: SHAKE WELL BEFORE EACH USE. Apply to dry coat. Dispense one or two pumps in your palm. Massage foam deep into pet's hair coat to ensure product reaches the skin. Repeat as many times as necessary to cover the whole body, or affected areas, as directed by your veterinarian. Avoid the eyes and mouth. Do not rinse. Let air dry. Once dry, brush the hair coat.

PRECAUTIONS

Caution: For topical use only. Avoid contact with eyes. If skin irritation develops or increases, stop use and call your veterinarian. Keep out of the reach of children and pets.

SAFE HANDLING WARNING

Human Warning: Wash hands after use. Rare but serious allergic reactions have been reported with exposure to chlorhexidine gluconate.

STORAGE AND HANDLING

Store at room temperature.

Available through licensed veterinarians.

For Veterinary Use Only.

Manufactured for:
Dechra Veterinary Products
7015 College Blvd.
Overland Park, KS 66211
(866) 933-2472

www.dechra-us.com

TCMW REV12/24-C

PRINCIPAL DISPLAY PANEL - 210 mL Bottle Label

SHAKE WELL BEFORE USING

TrizCHLOR® 4

Mousse
4% Chlorhexidine
Gluconate, USP
Formulated for dogs,
cats and horses
Antimicrobial, antibiofilm

7.1 fl. oz. (210 mL)
Dechra